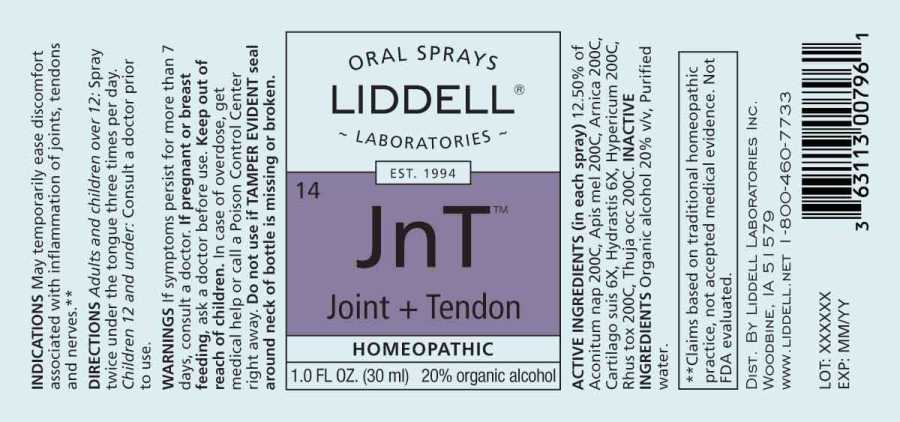 DRUG LABEL: Joint plus Tendon
NDC: 50845-0273 | Form: SPRAY
Manufacturer: Liddell Laboratories, Inc.
Category: homeopathic | Type: HUMAN OTC DRUG LABEL
Date: 20241104

ACTIVE INGREDIENTS: ACONITUM NAPELLUS WHOLE 200 [hp_C]/1 mL; APIS MELLIFERA 200 [hp_C]/1 mL; ARNICA MONTANA WHOLE 200 [hp_C]/1 mL; SUS SCROFA CARTILAGE 6 [hp_X]/1 mL; GOLDENSEAL 6 [hp_X]/1 mL; HYPERICUM PERFORATUM WHOLE 200 [hp_C]/1 mL; TOXICODENDRON PUBESCENS LEAF 200 [hp_C]/1 mL; THUJA OCCIDENTALIS LEAFY TWIG 200 [hp_C]/1 mL
INACTIVE INGREDIENTS: WATER; ALCOHOL

DRUG FACTS:

ACTIVE INGREDIENTS:

(in each spray) 12.50% of Aconitum Napellus 200C, Apis Mellifica 200C, Arnica Montana 200C, Cartilago Suis 6X, Hydrastis Canadensis 6X, Hypericum Perforatum 200C, Rhus Tox 200C, Thuja Occidentalis 200C.

INDICATIONS:

May temporarily ease discomfort associated with inflammation of joints, tendons and nerves.**

**Claims based on traditional homeopathic practice, not accepted medical evidence. Not FDA evaluated.

WARNINGS:

If symptoms persist for more than 7 days, consult a doctor.

If pregnant or breast feeding, ask a doctor before use.

Keep out of reach of children. In case of overdose, get medical help or call a Poison Control Center right away.

Do not use if TAMPER EVIDENT seal around neck of bottle is missing or broken.

Keep out of reach of children. In case of overdose, get medical help or call a Poison Control Center right away.

DIRECTIONS:

Adults and children over 12: Spray twice under the tongue 3 times per day.

Children 12 and under: Consult a doctor prior to use.

INDICATIONS:

May temporarily ease discomfort associated with inflammation of joints, tendons and nerves.**

**Claims based on traditional homeopathic practice, not accepted medical evidence. Not FDA evaluated.

INACTIVE INGREDIENTS:

Organic alcohol 20% v/v, Purified water.

QUESTIONS:

DIST. BY LIDDELL LABORATORIES INC.

WOODBINE, IA 51579

WWW.LIDDELL.NET 1-800-460-7733

PACKAGE LABEL DISPLAY:

ORAL SPRAYS
LIDDELL
LABORATORIES
EST. 1994
14 JnT
Joint + Tendon
HOMEOPATHIC
1.0 FL. OZ. (30 ml)